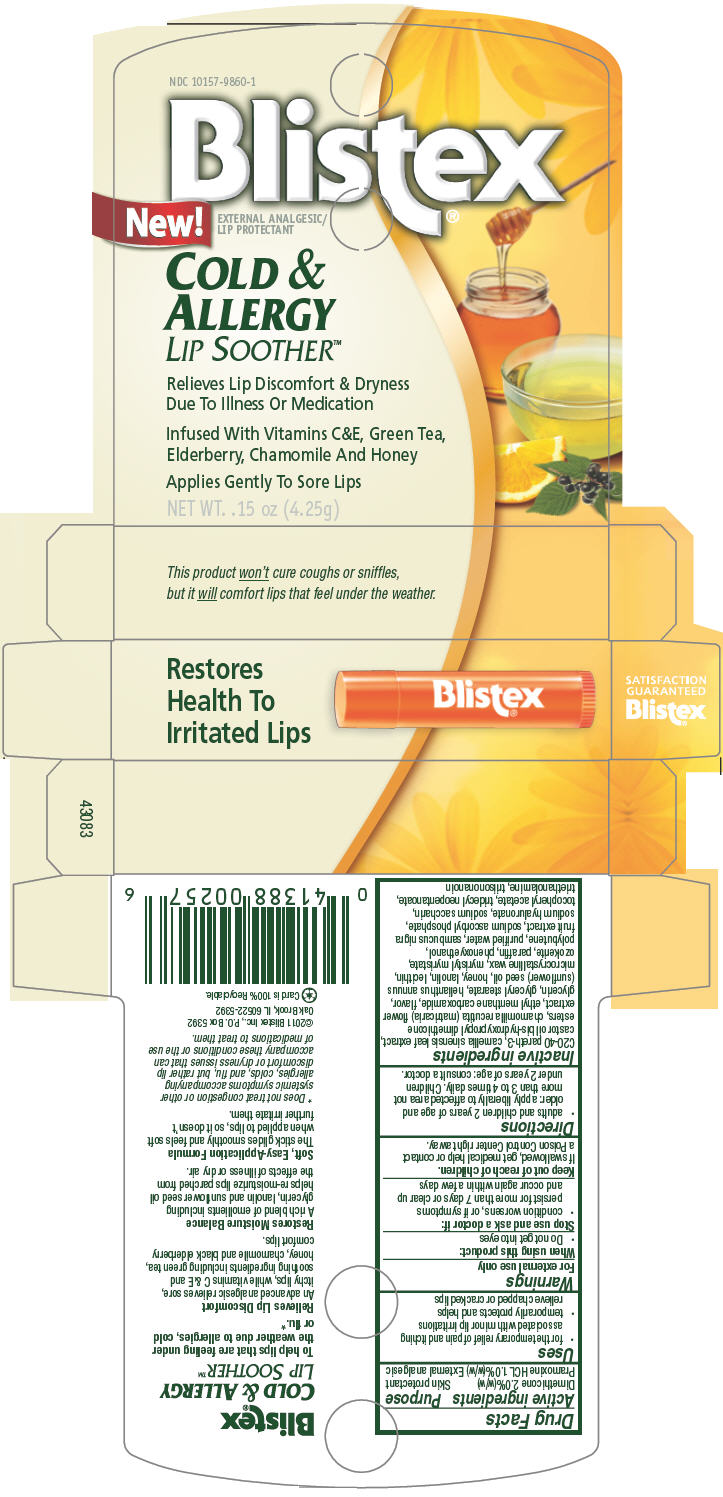 DRUG LABEL: Blistex 
NDC: 10157-9860 | Form: STICK
Manufacturer: Blistex Inc
Category: otc | Type: HUMAN OTC DRUG LABEL
Date: 20110912

ACTIVE INGREDIENTS: Dimethicone 2 g/100 g; Pramoxine Hydrochloride 1 g/100 g
INACTIVE INGREDIENTS: green tea leaf; chamomile; ethyl menthane carboxamide; glycerin; glyceryl monostearate; sunflower oil; honey; lanolin; microcrystalline wax; myristyl myristate; paraffin; phenoxyethanol; water; european elderberry; sodium ascorbyl phosphate; hyaluronate sodium; saccharin sodium; tridecyl neopentanoate; tangerine; ceresin; trolamine

Blistex®
COLD & ALLERGY
LIP SOOTHER™

Drug Facts

ACTIVE INGREDIENT

Active ingredients | Purpose
Dimethicone 2.0%(w/w) | Skin protectant
Pramoxine HCL 1.0%(w/w) | External analgesic

Uses

- for the temporary relief of pain and itching associated with minor lip irritations
- temporarily protects and helps relieve chapped or cracked lips

Warnings

For external use only

When using this product

- Do not get into eyes

Stop use and ask a doctor if

- condition worsens, or if symptoms persist for more than 7 days or clear up and occur again within a few days

Keep out of reach of children.

If swallowed, get medical help or contact a Poison Control Center right away.

Directions

- adults and children 2 years of age and older: apply liberally to affected area not more than 3 to 4 times daily. Children under 2 years of age: consult a doctor.

Inactive ingredients

C20-40 pareth-3, camellia sinensis leaf extract, castor oil bis-hydroxypropyl dimethicone esters, chamomilla recutita (matricaria) flower extract, ethyl menthane carboxamide, flavor, glycerin, glyceryl stearate, helianthus annuus (sunflower) seed oil, honey, lanolin, lecithin, microcrystalline wax, myristyl myristate, ozokerite, paraffin, phenoxyethanol, polybutene, purified water, sambucus nigra fruit extract, sodium ascorbyl phosphate, sodium hyaluronate, sodium saccharin, tocopheryl acetate, tridecyl neopentanoate, triethanolamine, triisononanoin

PRINCIPAL DISPLAY PANEL 4.25g Carton

NDC 10157-9860-1

Blistex®
New!
EXTERNAL ANALGESIC/
LIP PROTECTANT

COLD &
ALLERGY
LIP SOOTHER™

Relieves Lip Discomfort & Dryness
Due To Illness Or Medication

Infused With Vitamins C&E, Green Tea,
Elderberry, Chamomile And Honey

Applies Gently To Sore Lips

NET WT. .15 oz (4.25g)